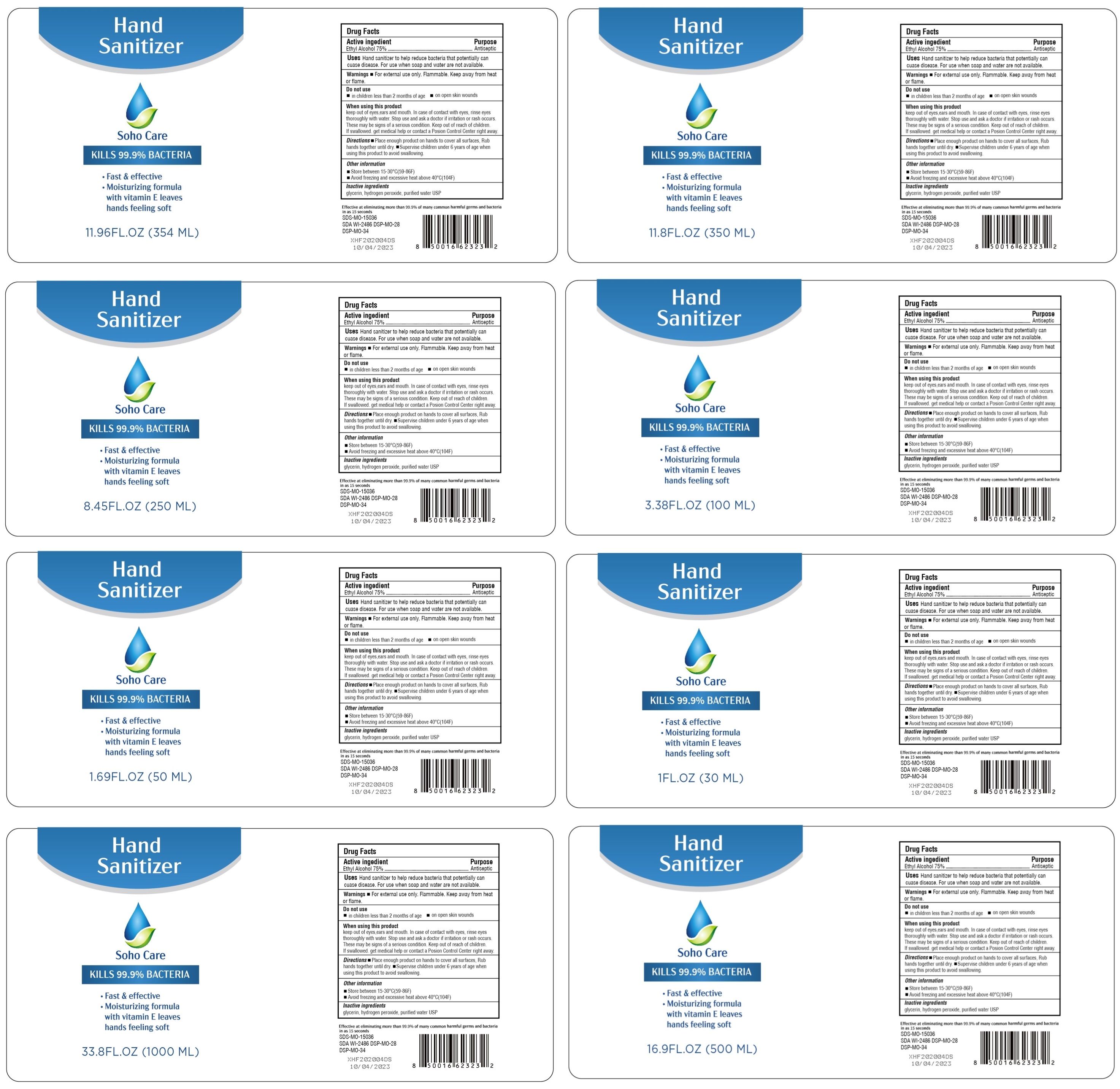 DRUG LABEL: Hand Sanitizer
NDC: 78414-002 | Form: GEL
Manufacturer: Guangzhou caolvxiang Biotechnology Co.,Ltd
Category: otc | Type: HUMAN OTC DRUG LABEL
Date: 20200714

ACTIVE INGREDIENTS: ALCOHOL 75 mL/100 mL
INACTIVE INGREDIENTS: HYDROGEN PEROXIDE; GLYCERIN; WATER

Hand Sanitizer

Active Ingredient(s)

Ethyl Alcohol 75%

Purpose

Antiseptic

Use

Hand sanitizer to help reduce bacteria that poterntially can cuase disease. For use when soap and water are not available.

Warnings

For external use only. Flammable. Keep away from heat or flame.

Do not use

in children less than 2 rnonths of age
on open skin worunds

WHEN USING SECTION

keep out of eyes.ears and mouth. In case of contact with eyes, rinse eyes thoroughly with water.

STOP USE

Stop use and ask a doctor if irritation or rash occurs.
These rnay be signs of a serious condition.

Keep out of reach of children

If swallowed. get medical help or contact a Posion Control Center right away.

Directions

Place enough product on hands to cover all surfaces, Rub hands together until dry.
Supervise clhildren under 6 years of age when using this product to avoid swallowing.

Other information

Store between 15-30°C(59-86F)
Avoid freezing and excessive heat above 40°C(104F)

Inactive ingredients

glycerin, hydrogen peroxide, purified water USP